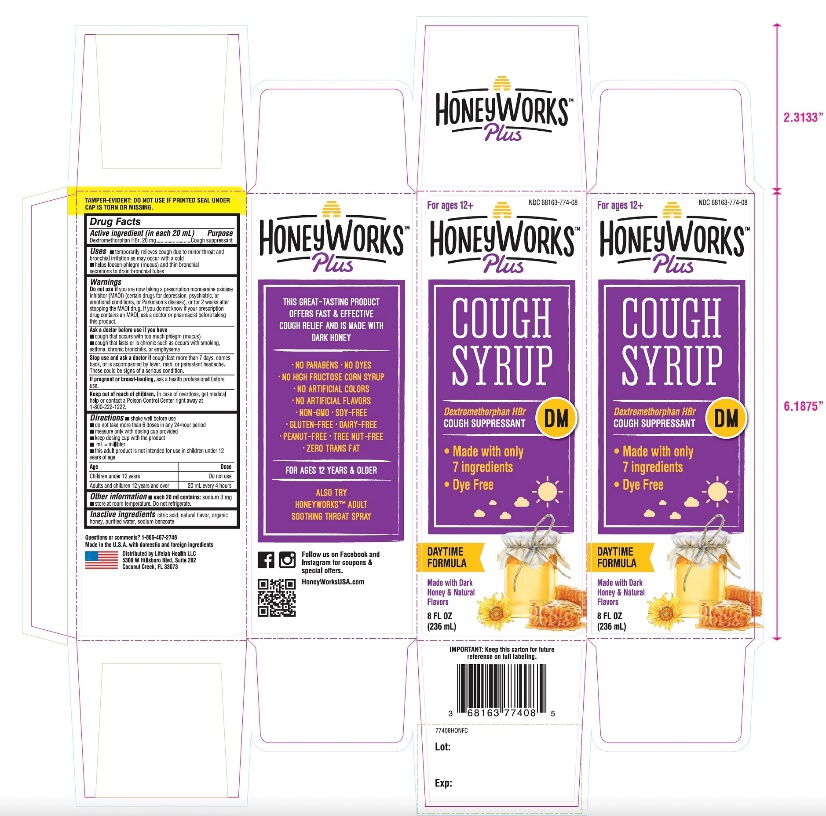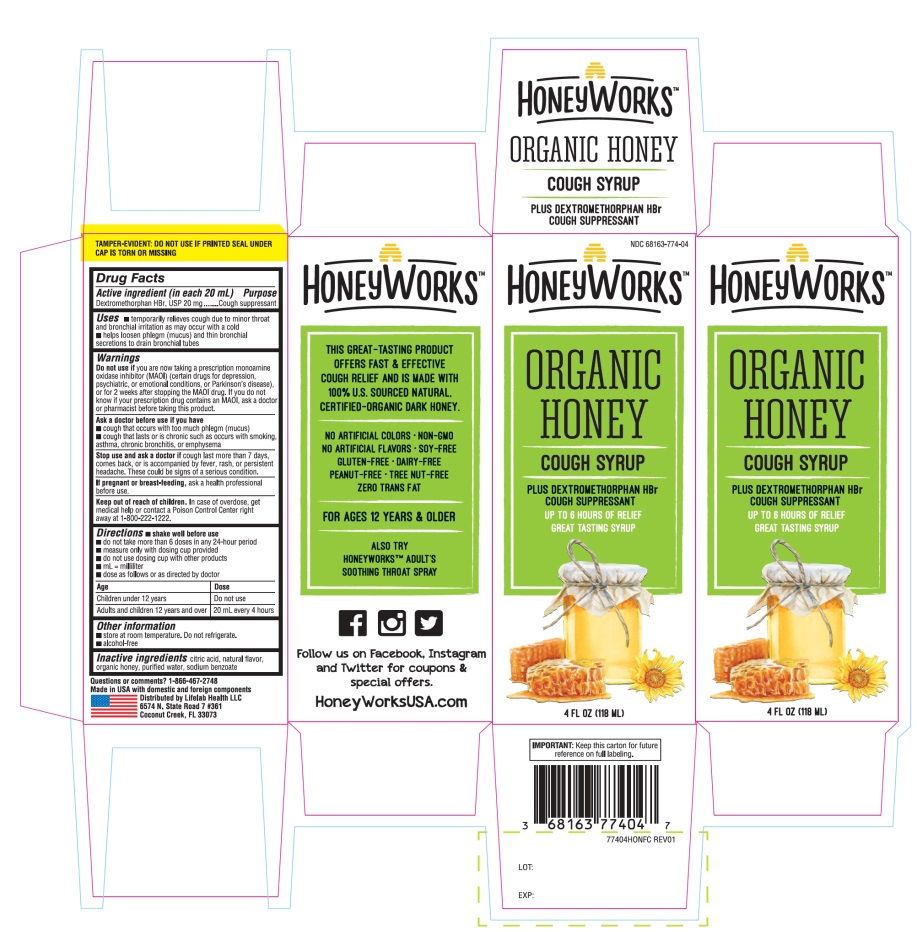 DRUG LABEL: Honey Works

NDC: 68163-774 | Form: SYRUP
Manufacturer: RARITAN PHARMACEUTICALS INC
Category: otc | Type: HUMAN OTC DRUG LABEL
Date: 20251014

ACTIVE INGREDIENTS: DEXTROMETHORPHAN HYDROBROMIDE 20 mg/20 mL
INACTIVE INGREDIENTS: ANHYDROUS CITRIC ACID; HONEY; WATER; SODIUM BENZOATE

Honey Works™ Organic Honey Cough Syrup

INDICATIONS AND USAGE

Active Ingredient (in each 20 mL)

Dextromethorphan HBr, USP 20 mg

Purpose

- Cough suppressant

Uses

- temporarily relieves cough due to minor throat and bronchial irritation as may occur with a cold
- helps loosen phlegm (mucus) and thin bronchial secretions to drain bronchial tubes

Warnings

DO NOT USE

Do not useif you are now taking a prescription monoamine oxidase inhibitor (MAOI) (certain drugs for depression, psychiatric, or emotional conditions, or Parkinson's disease), or for 2 weeks after stopping the MAOI drug. If you do not know if your prescription drug contains an MAOI, ask a doctor or pharmacist before taking this product.

Ask a doctor before use if you have

- cough that occurs with too much phlegm (mucus)
- cough that lasts or is chronic such as occurs with smoking, asthma, chronic bronchitis, or emphysema

Stop use and ask a doctor ifcough lasts more than 7 days, comes back, or is accompanied by fever, rash, or persistent headache. These could be signs of a serious condition.

PREGNANCY OR BREAST FEEDING

If pregnant or breast-feeding,ask a health professional before use.

Keep out of reach of children.In case of overdose, get medical help or contact a Poison Control Center right away at 1-800-222-1222.

Directions

- shake well before use
- do not take more than 6 doses in any 24-hour period
- measure only with dosing cup provided
- keep dosing cup with product
- ml = milliliter
- doses as follows or as directed by doctor

age | dose
children 12 years | Do not use
Adults and children 12 years and over | 20 mL every 4 hours

Other information

- store at room temperature
- alcohol free

Inactive ingredients

citric acid, natural and artificial flavors, organic honey, purified water, sodium benzoate.

Questions or comments?

1-866-467-2748

PRINCIPAL DISPLAY PANEL - 118 ml Bottle Label

NDC# 68163-774-04

Honey Works™

ORGANIC HONEY

COUGH SYRUP

PLUS DEXTROMETHORPHAN HBr

COUGH SUPPRESSANT

UP TO 6 HOURS OF RELIEF GREAT TASTING SYRUP

4 FL OZ (118 ml)

THIS GREAT- TASTING PRODUCT OFFERS FAST & EFFECTIVE COUGH RELIEF AND IS MADE WITH 100% U.S. SOURCED NATURAL CERTIFIED-ORGANIC DARK HONEY.

- NO ARTIFICIAL COLORS
- NON-GMO
- NO ARTIFICIAL FLAVOR
- SOY-FREE
- GLUTEN-FREE
- DAIRY-FREE
- PEANUT-FREE
- TREE NUT-FREE
- ZERO TRANS FAT

FOR AGES 12 YEARS & OLDER

ALSO TRY HONEYWORKS™ ADULTS SOOTHING THROAT SPRAY

Made in USA with domestic and foreign components

Distributed by: Lifelab Health LLC

6574 N. State Road 7 #361

Coconut Creek, FL 33073

IMPORTANT: Keep this carton for future reference on full labeling.

Package Label for 8 OZ